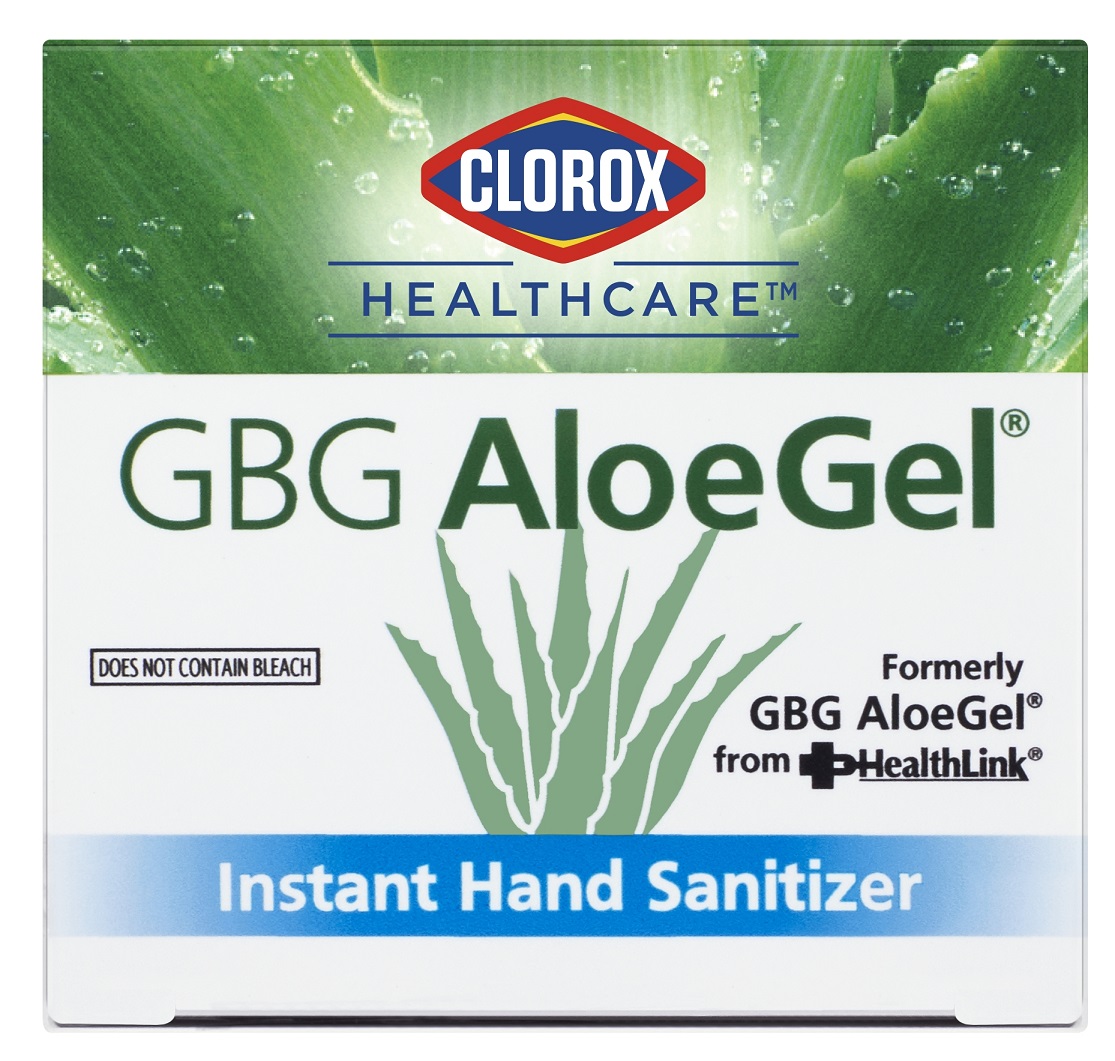 DRUG LABEL: Clorox HealthCare GBG AloeGel Instant Hand Sanitizer
NDC: 69540-0026 | Form: GEL
Manufacturer: Brand Buzz LLC
Category: otc | Type: HUMAN OTC DRUG LABEL
Date: 20230202

ACTIVE INGREDIENTS: ALCOHOL 71 mL/100 mL
INACTIVE INGREDIENTS: FD&C YELLOW NO. 5; ISOPROPYL MYRISTATE; .ALPHA.-TOCOPHEROL ACETATE; TROLAMINE; GLYCERIN; ALOE VERA LEAF; D&C YELLOW NO. 10; CARBOMER INTERPOLYMER TYPE A (ALLYL SUCROSE CROSSLINKED); GLYCERETH-2 COCOATE; FD&C BLUE NO. 1; WATER

Clorox HealthCare GBG AloeGel Instant Hand Sanitizer

Active ingredient

Ethanol 64% w/w

Purpose

Antiseptic

Uses

- for hand-washing to decrease bacteria on the skin when water is not available

Warnings

FLAMMABLE. Keep away from fire or flame

For external use only

When using this product

- do not use in or near eyes
- discontinue use if irritation andredness develop
- do not use on deep or puncture woulds; consult your doctor

Keep out of reach of children.

In case of accidental ingestion, seek medical attention or contact a poison control center immediately.

Directions

- apply gel liberally to unsoiled hands and rub thoroughly
- allow to dry without wiping or rinsing

Other information

- store at room temperature

Inactive ingredients

Acrylates/C10-30 Alkyl Acrylate Crosspolymer. Aloe Barbadensis Leaf Juice, D&C Yellow #10, FD&C Blue #1, FD&C Yellow #5, Fragrance, Glycereth-2 Cocoate, Glycerin, Isopropyl Myristate, Tocopheryl Acetate, Triethanolamine, Water

Package Label: 118ml/532ml/800ml

CLOROX

HEALTHCARE

GBG Aloe Gel

Does Not Contain Bleach

Formerly

GBG AloeGel

from HealthLink

Instant Hand Sanitizer